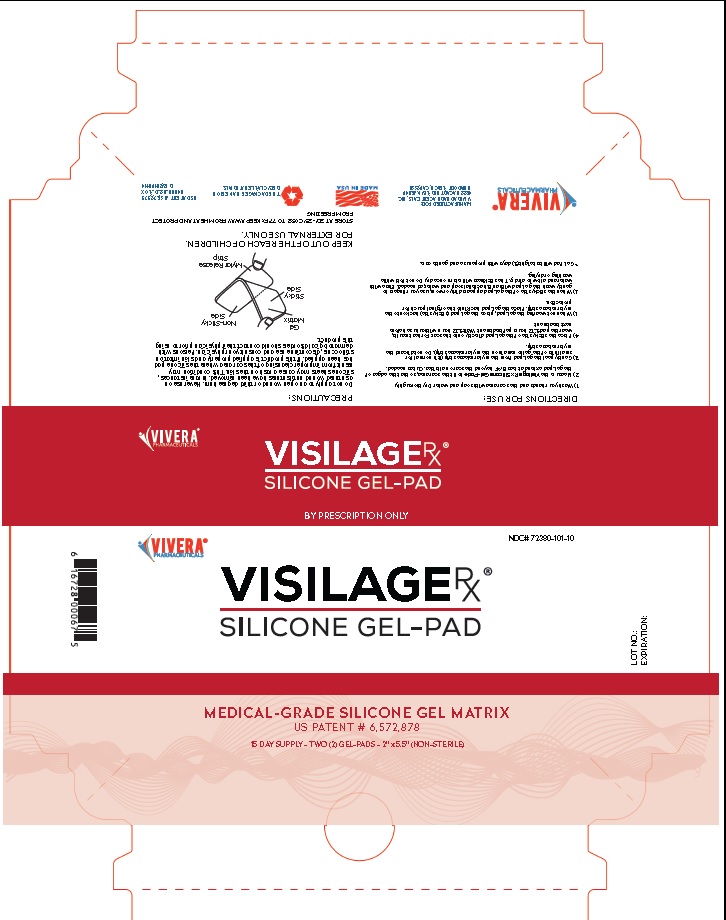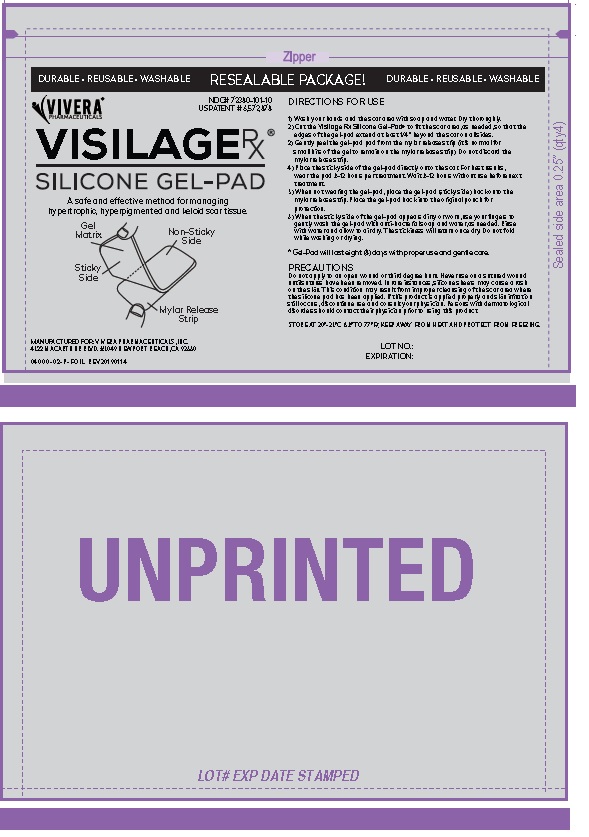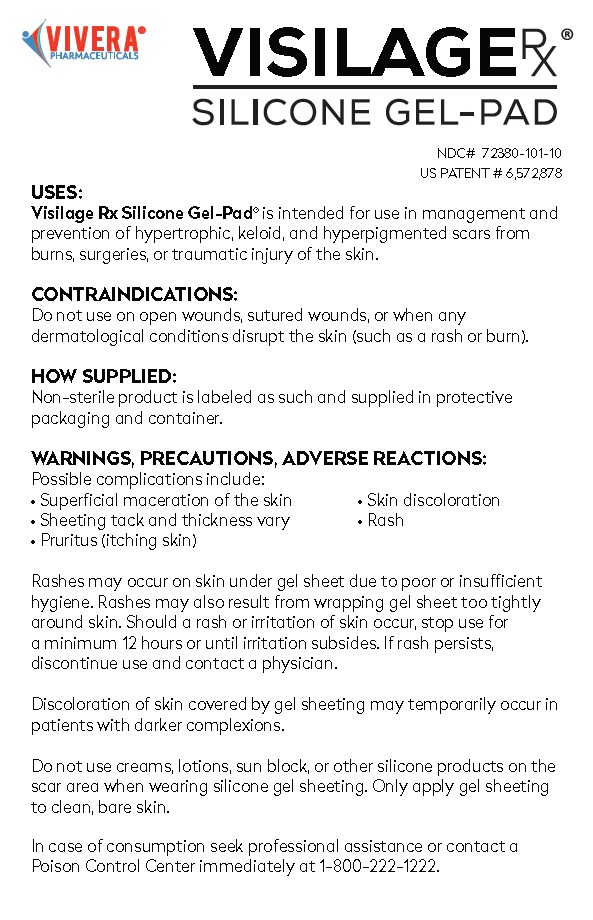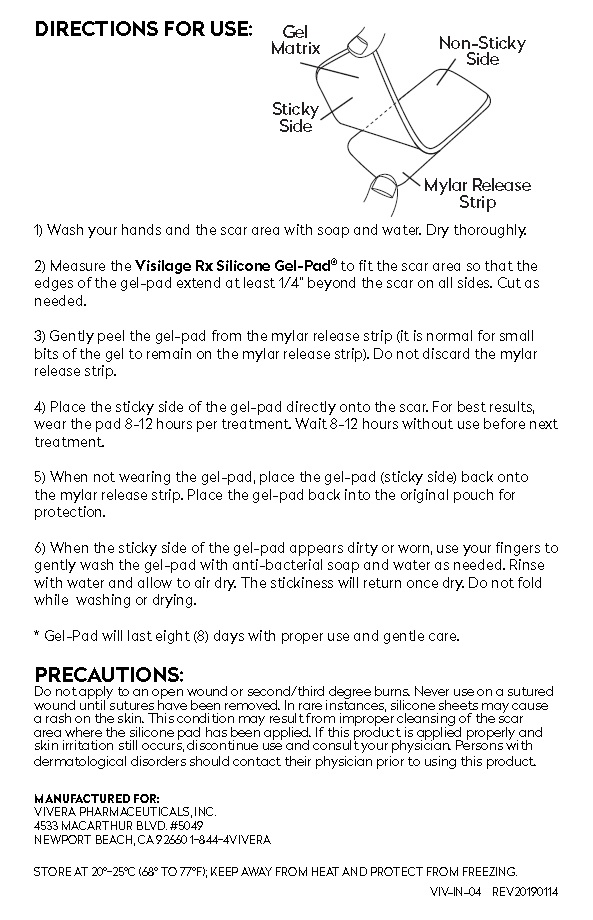 DRUG LABEL: VISILAGE RX SILICONE GEL-PAD
NDC: 72380-101
Manufacturer: Vivera Pharmaceuticals, Inc.
Category: other | Type: MEDICAL DEVICE
Date: 20181204

VISILAGE RX SILICONE GEL-PAD

VISILAGE RX®
SILICONE GEL-PAD

BY PRESCRIPTION ONLY

USES:
Visilage RX Silicone Gel-Pad® is intended for use in management and
prevention of hypertrophic, keloid, and hyperpigmented scars from burns,
surgeries, or traumatic injury of the skin.

CONTRAINDICATIONS:
Do not use on open wounds, sutured wounds, or when any
dermatological conditions disrupt the skin (such as a rash or burn).

HOW SUPPLIED:
Non-sterile product is labeled as such and supplied in protective
packaging and container.

WARNINGS, PRECAUTIONS, ADVERSE REACTIONS:
Possible complications include:
• Superficial maceration of the skin • Skin discoloration
• Sheeting tack and thickness vary • Rash
• Pruritus (itching skin)

Rashes may occur on skin under gel sheet due to poor or insufficient
hygiene. Rashes may also result from wrapping gel sheet too tightly
around skin. Should a rash or irritation of skin occur, stop use for a
minimum 12 hours or until irritation subsides. If rash persists, discontinue
use and contact a physician.

Discoloration of skin covered by gel sheeting may temporarily occur in
patients with darker complexions.

Do not use creams, lotions, sun block, or other silicone products on your
skin when wearing silicone gel sheeting. Only apply gel sheeting to clean,
bare skin.

In case of consumption seek professional assistance or contact a
Poison Control Center immediately at 1-800-222-1222.

INDICATIONS AND USAGE

DIRECTIONS FOR USE:
1) Wash your hands and the scar area with soap and water. Dry thoroughly.

2) Measure the Visilage Rx Silicone Gel-Pad® to fit the scar area so that the
edges of the gel-pad extend at least 1/4” beyond the scar on all sides. Cut as
needed.

3) Gently peel the gel-pad from the mylar release strip (it is normal for small
bits of the gel to remain on the mylar release strip). Do not discard the mylar
release strip.

4) Place the sticky side of the gel-pad directly onto the scar. For best results,
wear the pad 8-12 hours per treatment. Wait 8-12 hours without use before
next treatment.

5) When not wearing the gel-pad, place the gel-pad (sticky side) back onto
the mylar release strip. Place the gel-pad back into the original pouch for
protection.

6) When the sticky side of the gel-pad appears dirty or worn, use your fingers
to gently wash the gel-pad with anti-bacterial soap and water as needed. Rinse
with water and allow to air dry. The stickiness will return once dry. Do not fold
while washing or drying.

* Gel-Pad will last eight (8) days with proper use and gentle care.

PRECAUTIONS:
Do not apply to an open wound or second/third degree burns. Never use on a sutured
wound until sutures have been removed. In rare instances, silicone sheets may cause
a rash on the skin. This condition may result from improper cleansing of the scar
area where the silicone pad has been applied. If this product is applied properly and
skin irritation still occurs, discontinue use and consult your physician. Persons with
dermatological disorders should contact their physician prior to using this product.

Principal Display Panel

VIVERA®
PHARMACEUTICALS

VISILAGE RX®
SILICONE GEL-PAD

BY PRESCRIPTION ONLY

VIVERA®
PHARMACEUTICALS

NDC# 72380-101-10

VISILAGE RX®
SILICONE GEL-PAD

LOT NO.:
EXPIRATION:

MEDICAL-GRADE SILICONE GEL MATRIX
US PATENT # 6,572,878
15 DAY SUPPLY - TWO (2) GEL-PADS - 2” x 5.5” (NON-STERILE)

6 16728 00067 5

DIRECTIONS FOR USE:
1) Wash your hands and the scar area with soap and water. Dry thoroughly.

2) Measure the Visilage Rx Silicone Gel-Pad® to fit the scar area so that the
edges of the gel-pad extend at least 1/4” beyond the scar on all sides. Cut as
needed.

3) Gently peel the gel-pad from the mylar release strip (it is normal for small
bits of the gel to remain on the mylar release strip). Do not discard the mylar
release strip.

4) Place the sticky side of the gel-pad directly onto the scar. For best results,
wear the pad 8-12 hours per treatment. Wait 8-12 hours without use before
next treatment.

5) When not wearing the gel-pad, place the gel-pad (sticky side) back onto
the mylar release strip. Place the gel-pad back into the original pouch for
protection.

6) When the sticky side of the gel-pad appears dirty or worn, use your fingers
to gently wash the gel-pad with anti-bacterial soap and water as needed. Rinse
with water and allow to air dry. The stickiness will return once dry. Do not fold
while washing or drying.

* Gel-Pad will last eight (8) days with proper use and gentle care.

PRECAUTIONS:
Do not apply to an open wound or third degree burn. Never use on a sutured
wound until sutures have been removed. In rare instances, silicone sheets
may cause a rash on the skin. This condition may result from improper
cleansing of the scar area where the silicone pad has been applied. If this
product is applied properly and skin irritation still occurs, discontinue use and
consult your physician. Persons with dermatological disorders should contact
their physician prior to using this product.

KEEP OUT OF THE REACH OF CHILDREN.
FOR EXTERNAL USE ONLY.

STORE AT 20°-25°C (68° TO 77°F); KEEP AWAY FROM HEAT AND PROTECT
FROM FREEZING.

VIVERA®
PHARMACEUTICALS

MANUFACTURED FOR:
VIVERA PHARMACEUTICALS, INC.
4533 MACARTHUR BLVD. #5049
NEWPORT BEACH, CA 92660

MADE IN USA

THIS PACKAGE IS MADE FROM
RECYCLABLE MATERIALS.

US PATENT # 6,572,878
04000-03-P-BOX
REV20190114

↓Pouch Label↓

↓Patient Insert↓

Visilage Rx® Silicone Gel-Pad by Vivera Pharmaceuticals, Inc.

res